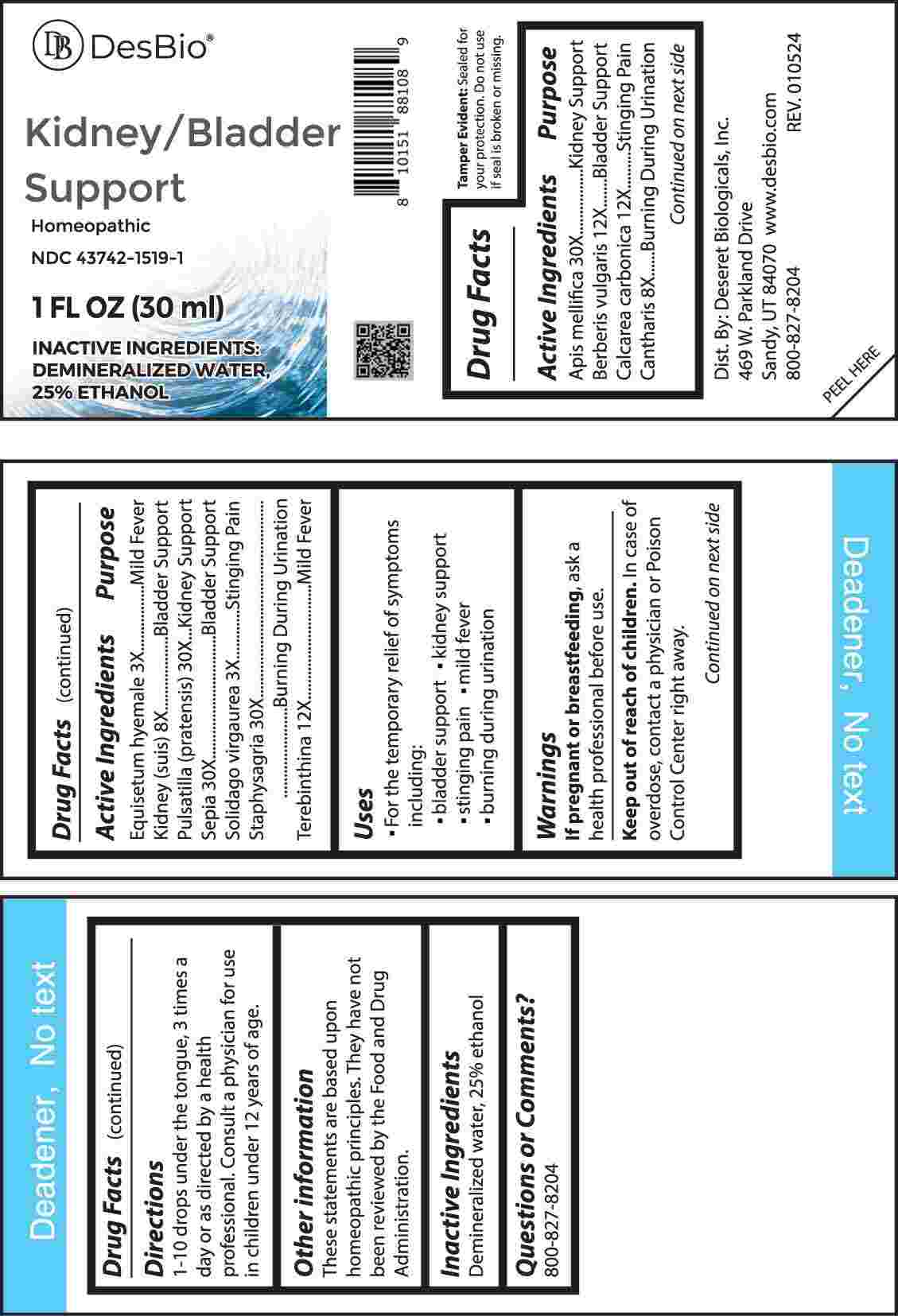 DRUG LABEL: Kidney/Bladder Support
NDC: 43742-1519 | Form: LIQUID
Manufacturer: Deseret Biologicals, Inc.
Category: homeopathic | Type: HUMAN OTC DRUG LABEL
Date: 20240417

ACTIVE INGREDIENTS: EQUISETUM HYEMALE WHOLE 3 [hp_X]/1 mL; SOLIDAGO VIRGAUREA FLOWERING TOP 3 [hp_X]/1 mL; LYTTA VESICATORIA 8 [hp_X]/1 mL; PORK KIDNEY 8 [hp_X]/1 mL; BERBERIS VULGARIS ROOT BARK 12 [hp_X]/1 mL; OYSTER SHELL CALCIUM CARBONATE, CRUDE 12 [hp_X]/1 mL; TURPENTINE OIL 12 [hp_X]/1 mL; APIS MELLIFERA 30 [hp_X]/1 mL; PULSATILLA PRATENSIS WHOLE 30 [hp_X]/1 mL; SEPIA OFFICINALIS JUICE 30 [hp_X]/1 mL; DELPHINIUM STAPHISAGRIA SEED 30 [hp_X]/1 mL
INACTIVE INGREDIENTS: WATER; ALCOHOL

DRUG FACTS:

ACTIVE INGREDIENTS:

Apis Mellifica 30X, Berberis Vulgaris 12X, Calcarea Carbonica 12X, Cantharis 8X, Equisetum Hyemale 3X, Kidney (Suis) 8X, Pulsatilla (Pratensis) 30X, Sepia 30X, Solidago Virgaurea 3X, Staphysagria 30X, Terebinthina 12X.

PURPOSE:

Apis Mellifica – Kidney Support, Berberis Vulgaris – Bladder Support, Calcarea Carbonica – Stinging Pain, Cantharis – Burning During Urination, Equisetum Hyemale – Mild Fever, Kidney (Suis) – Bladder Support, Pulsatilla (Pratensis) – Kidney Support, Sepia – Bladder Support, Solidago Virgaurea – Stinging Pain, Staphysagria – Burning During Urination, Terebinthina – Mild Fever

USES:

• For the temporary relief of symptoms including:

• bladder support • kidney support • stinging pain

• mild fever • burning during urination

These statements are based upon homeopathic principles. They have not been reviewed by the Food and Drug Administration.

WARNINGS:

If pregnant or breast-feeding, ask a health professional before use.

Keep out of reach of children. In case of overdose, contact a physician or Poison Control Center right away.

Tamper Evident: Sealed for your protection. Do not use if seal is broken or missing.

KEEP OUT OF REACH OF CHILDREN:

In case of overdose, contact a physician or Poison Control Center right away.

DIRECTIONS:

10 drops under the tongue, 3 times a day or as directed by a health professional. Consult a physician for use in children under 12 years of age.

INACTIVE INGREDIENTS:

Demineralized water, 25% ethanol

QUESTIONS:

Dist. By: Deseret Biologicals, Inc.

469 W. Parkland Drive

Sandy, UT 84070

www.desbio.com

800-827-8204

PACKAGE LABEL DISPLAY:

Des Bio

Kidney/Bladder

Support

Homeopathic

NDC 43742-1519-1

1 FL OZ (30 ml)